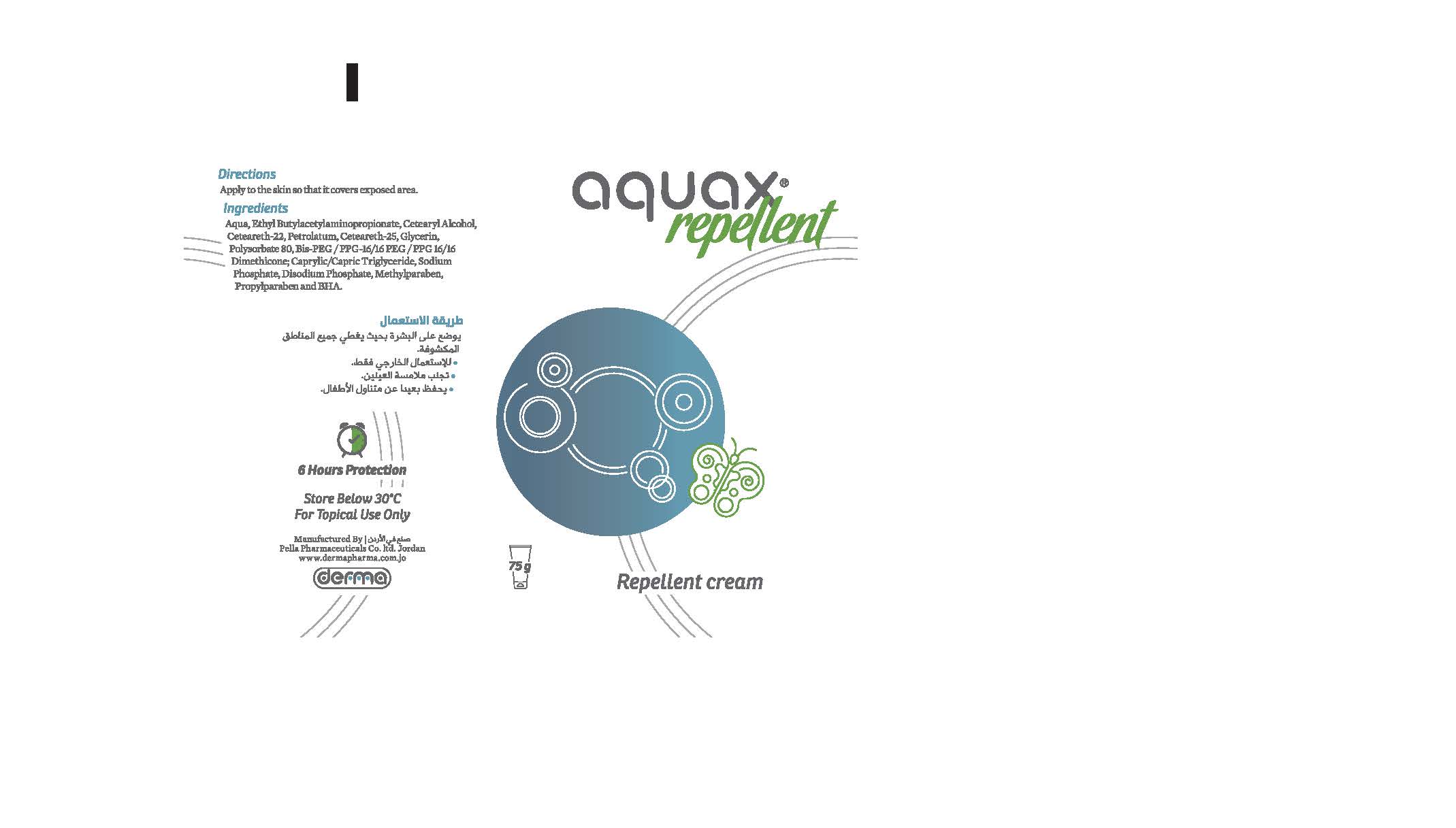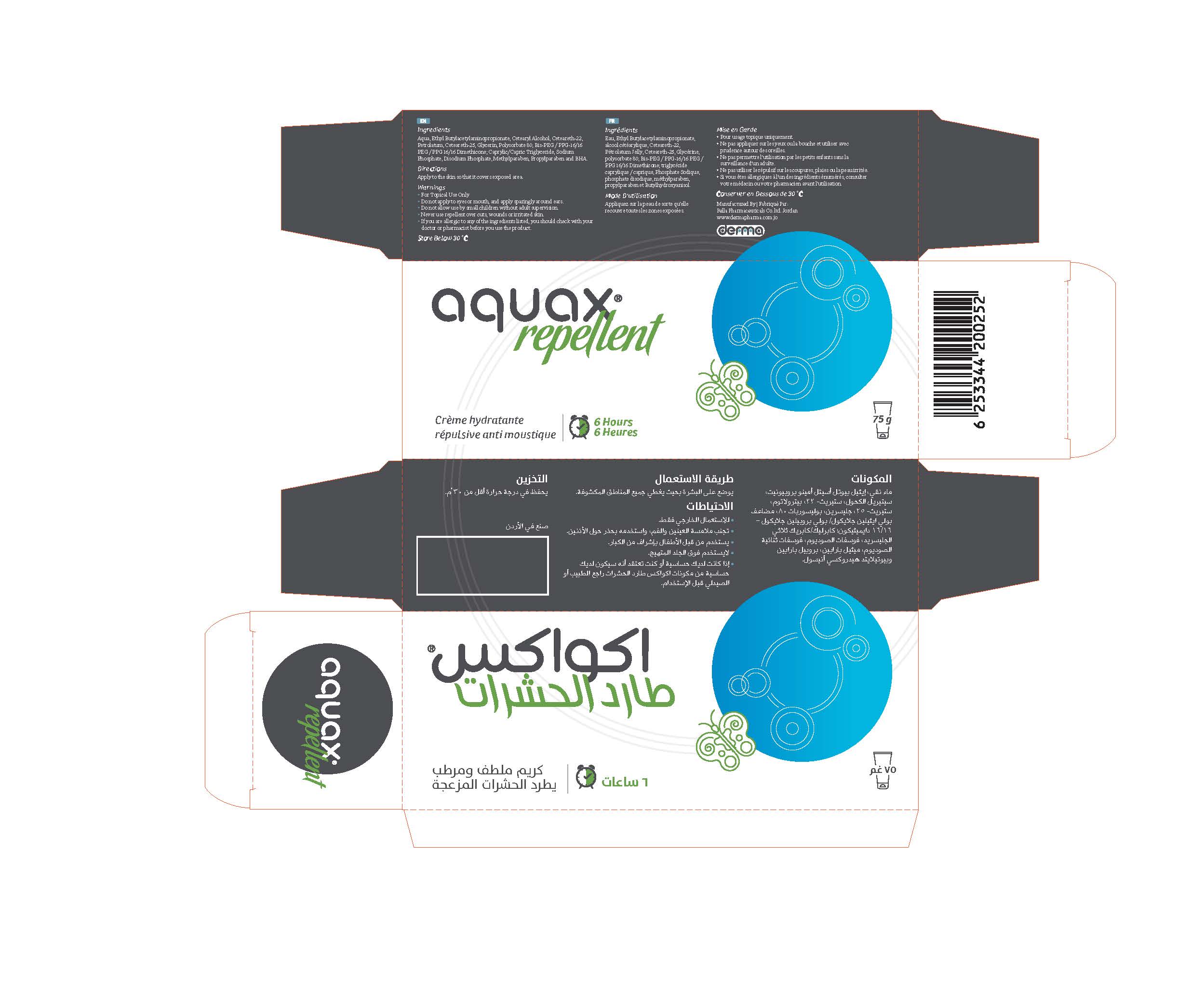 DRUG LABEL: Aquax Repellent
NDC: 82160-252 | Form: CREAM
Manufacturer: Pella Pharmaceuticals Co. Ltd
Category: otc | Type: HUMAN OTC DRUG LABEL
Date: 20211125

ACTIVE INGREDIENTS: ETHYL BUTYLACETYLAMINOPROPIONATE 75 mg/75 g
INACTIVE INGREDIENTS: MEDIUM-CHAIN TRIGLYCERIDES; PROPYLPARABEN; SODIUM PHOSPHATE, MONOBASIC; SODIUM PHOSPHATE, DIBASIC; WATER; POLYSORBATE 80; BIS-PEG/PPG-16/16 PEG/PPG-16/16 DIMETHICONE; BUTYLATED HYDROXYANISOLE; CETEARETH-25; GLYCERIN; METHYLPARABEN; CETOSTEARYL ALCOHOL; CETEARETH-22; PETROLATUM

Repellent

Forms and presentation

Cream: Tube of 75 g.

Active Ingredient

Ethyl Butylacetylaminopropionate

Inactive Ingredients

Aqua, Cetearyl Alcohol, Ceteareth-22, Petrolatum, Ceteareth-25, Glycerin, Polysorbate 80, Bis-PEG/ PPG-16/16 PEG/ PPG 16/16 Dimethicone; Caprylic/Capric Triglyceride, Sodium Phosphate, Disodium Phosphate, Methylparaben, Propylparaben and BHA.

Purpose

Insect repellent

Properties

Aquax® Repellent Cream is a cream that hydrates, nourishes, and expels the pesky insects.

Indications

Aquax® Repellent Cream hydrates the skin, decreases itchy sensation and provides the feeling of comfort. It's characterized by the presence of the active ingredient Ethyl Butylacetylaminopropionate (IR3535) that acts as a bio-pesticide, its efficacy as insect repellent endures for 6 hours long.

Precautions

Keep out of reach of children

Warnings

- For external use only.
- Do not apply to eyes or mouth, and apply sparingly around ears.
- Do not allow use by small children without adult supervision.
- Never use repellent over cuts, wounds or irritated skin.
- If you are allergic to any of the ingredients listed, you should check with your doctor or pharmacist before you use the product

Contraindications

Hypersensitivity to any of the components.

Side effects

Aquax® Repellent Cream has no known side effect, because its use is safe.
Preferably used by small children under the supervision of an adult.

Dosage and administration

Apply just enough Aquax® Repellent Cream to cover exposed skin.

Storage conditions

Store at a temperature below 30° C.